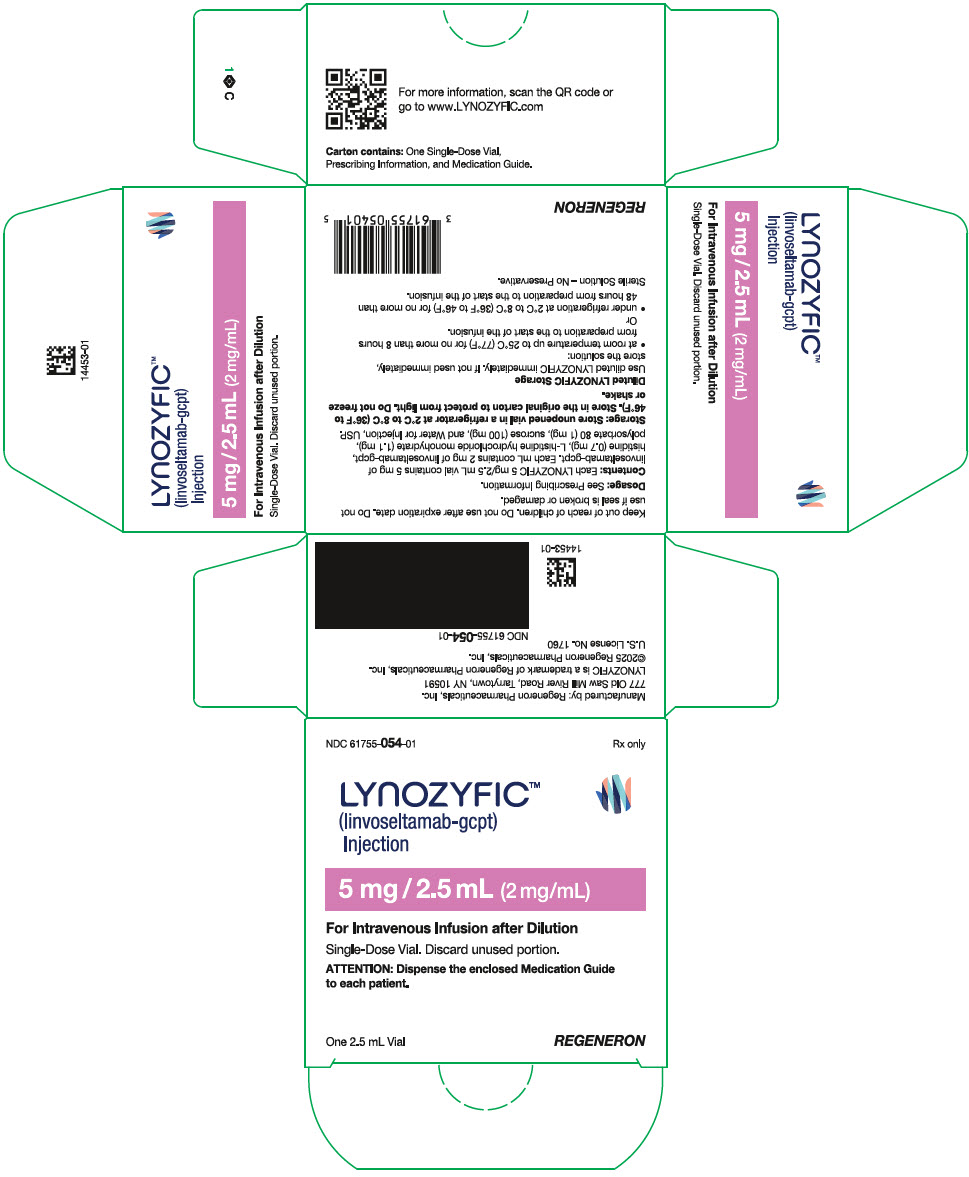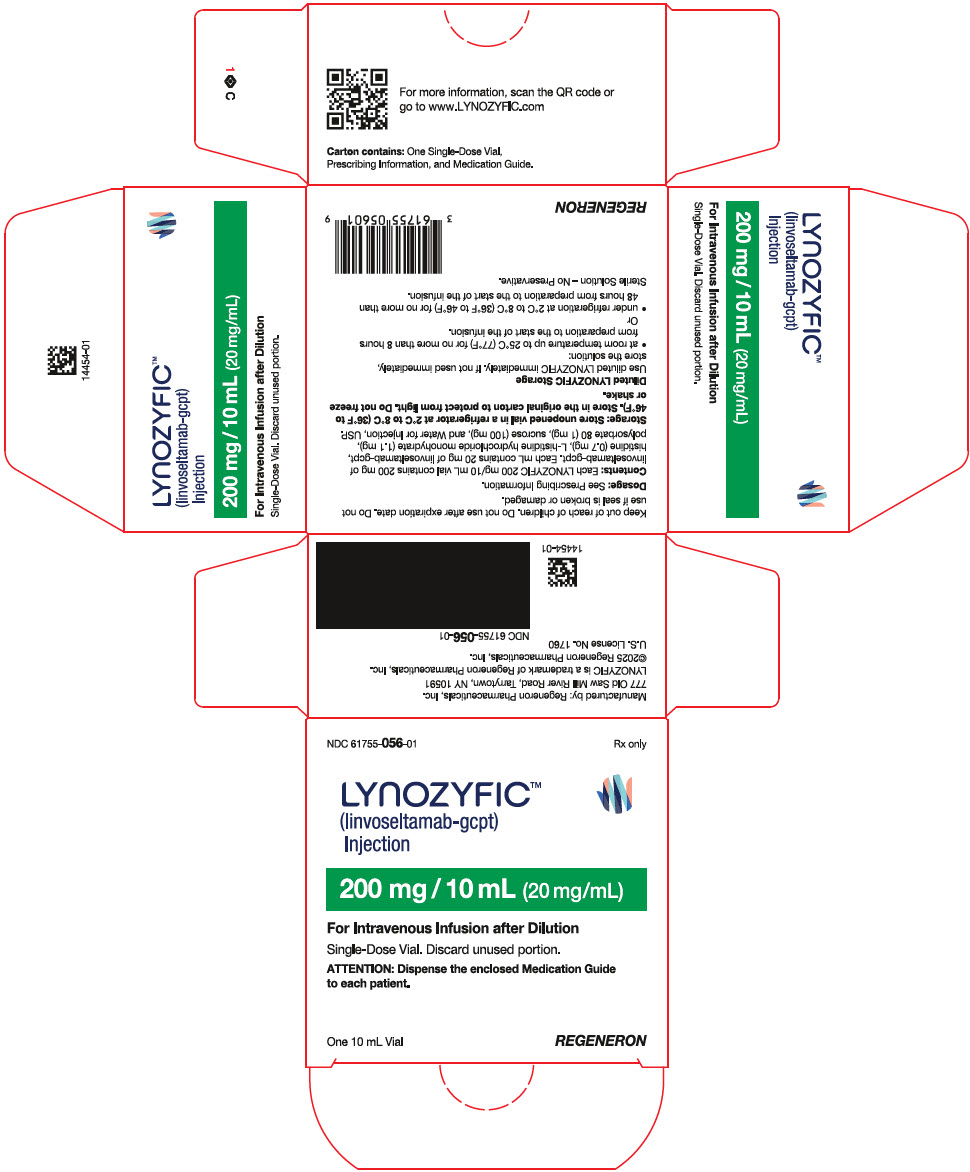 DRUG LABEL: LYNOZYFIC
NDC: 61755-054 | Form: INJECTION, SOLUTION, CONCENTRATE
Manufacturer: Regeneron Pharmaceuticals, Inc.
Category: prescription | Type: HUMAN PRESCRIPTION DRUG LABEL
Date: 20250702

ACTIVE INGREDIENTS: LINVOSELTAMAB 5 mg/2.5 mL
INACTIVE INGREDIENTS: HISTIDINE; HISTIDINE HYDROCHLORIDE MONOHYDRATE; POLYSORBATE 80; SUCROSE; WATER

HIGHLIGHTS OF PRESCRIBING INFORMATION

These highlights do not include all the information needed to use LYNOZYFIC safely and effectively. See full prescribing information for LYNOZYFIC.
LYNOZYFIC™ (linvoseltamab-gcpt) injection, for intravenous use
Initial U.S. Approval: 2025

WARNING: CYTOKINE RELEASE SYNDROME AND NEUROLOGIC TOXICITY, INCLUDING IMMUNE EFFECTOR CELL-ASSOCIATED NEUROTOXICITY SYNDROME

See full prescribing information for complete boxed warning.

- Cytokine release syndrome (CRS), including serious or life-threatening reactions, can occur in patients receiving LYNOZYFIC. Initiate treatment with LYNOZYFIC step-up dosing to reduce the risk of CRS. Manage CRS, withhold LYNOZYFIC until CRS resolves and modify the next dose or permanently discontinue based on severity. (2.2, 2.4, 2.5, 5.1)
- Neurologic Toxicity, including immune effector cell-associated neurotoxicity syndrome (ICANS), including serious or life-threatening reactions, can occur in patients receiving LYNOZYFIC. Monitor patients for signs or symptoms of neurologic toxicity, including ICANS during treatment. Manage neurologic toxicity, including ICANS, withhold LYNOZYFIC until neurologic toxicity, including ICANS resolves and modify the next dose or permanently discontinue based on severity. (2.2, 2.4, 2.5, 5.2)
- LYNOZYFIC is available only through a restricted program called the LYNOZYFIC Risk Evaluation and Mitigation Strategy (REMS). (5.3)

1 INDICATIONS AND USAGE

LYNOZYFIC is a bispecific B-cell maturation antigen (BCMA)‑directed CD3 T-cell engager indicated for the treatment of adult patients with relapsed or refractory multiple myeloma who have received at least four prior lines of therapy, including a proteasome inhibitor, an immunomodulatory agent, and an anti‑CD38 monoclonal antibody.

This indication is approved under accelerated approval based on response rate and durability of response. Continued approval for this indication may be contingent upon verification and description of clinical benefit in confirmatory trial(s). (1)

2 DOSAGE AND ADMINISTRATION

- Premedicate to reduce the risk of CRS and infusion-related reactions (IRR). (2.1, 2.3)
- Administer only as an intravenous infusion. (2.1, 2.6)
- Recommended Dosage (2.2):

Dosing Schedule | Day | Dose of LYNOZYFIC
Step-Up Dosing Schedule | Day 1 | Step-up dose 1 | 5 mg
Step-Up Dosing Schedule | Day 8 | Step-up dose 2 | 25 mg
Step-Up Dosing Schedule | Day 15 | First treatment dose | 200 mg
Weekly Dosing Schedule | One week after Day 15 treatment dose and once weekly from Week 4 to Week 13 for 10 treatment doses | Second and subsequent treatment doses | 200 mg
Biweekly (Every 2 Weeks) Dosing Schedule | Week 14 and every 2 weeks thereafter | Subsequent treatment doses | 200 mg
Patients who have achieved and maintained VGPR or better at or after Week 24 and received at least 17 doses of 200 mg
Every 4 Weeks Dosing Schedule | At Week 24 or after and every 4 weeks thereafter | Subsequent treatment doses | 200 mg

- Patients should be hospitalized for 24 hours after administration of the first step-up dose and for 24 hours after administration of the second step-up dose. (2.1)
- See Full Prescribing Information for instructions on preparation and administration. (2.6)

3 DOSAGE FORMS AND STRENGTHS

Injection:

- 5 mg/2.5 mL (2 mg/mL) single-dose vial (3)
- 200 mg/10 mL (20 mg/mL) single-dose vial (3)

4 CONTRAINDICATIONS

None. (4)

5 WARNINGS AND PRECAUTIONS

- Infections: Can cause serious or fatal infections. Monitor patients for signs or symptoms of infection and treat accordingly. (5.4)
- Neutropenia: Monitor complete blood cell counts at baseline and periodically during treatment. (5.5)
- Hepatotoxicity: Can cause hepatotoxicity. Monitor liver enzymes and bilirubin at baseline and during treatment as clinically indicated. (5.6)
- Embryo-Fetal Toxicity: May cause fetal harm. Advise females of reproductive potential of the potential risk to the fetus and to use effective contraception. (5.7, 8.1, 8.3)

6 ADVERSE REACTIONS

The most common adverse reactions (≥20%) are musculoskeletal pain, cytokine release syndrome, cough, upper respiratory tract infection, diarrhea, fatigue, pneumonia, nausea, headache, and dyspnea. (6.1)

The most common Grade 3 or 4 laboratory abnormalities (≥30%) are decreased lymphocyte count, decreased neutrophil count, decreased hemoglobin, and decreased white blood cell count. (6.1)

To report SUSPECTED ADVERSE REACTIONS, contact Regeneron at 1-844-467-2998 or FDA at 1-800-FDA-1088 or www.fda.gov/medwatch.

8 USE IN SPECIFIC POPULATIONS

Lactation: Advise not to breastfeed. (8.2)

FULL PRESCRIBING INFORMATION

WARNING: CYTOKINE RELEASE SYNDROME AND NEUROLOGIC TOXICITY, INCLUDING IMMUNE EFFECTOR CELL-ASSOCIATED NEUROTOXICITY SYNDROME

- Cytokine release syndrome (CRS), including serious or life-threatening reactions, can occur in patients receiving LYNOZYFIC. Initiate treatment with LYNOZYFIC step-up dosing to reduce the risk of CRS. Manage CRS, withhold LYNOZYFIC until CRS resolves, and modify the next dose or permanently discontinue based on severity [see Dosage and Administration (2.2, 2.4, 2.5) and Warnings and Precautions (5.1)].
- Neurologic toxicity, including immune effector cell-associated neurotoxicity syndrome (ICANS), including serious or life-threatening reactions, can occur in patients receiving LYNOZYFIC. Monitor patients for signs or symptoms of neurologic toxicity, including ICANS during treatment. Manage neurologic toxicity, including ICANS, withhold LYNOZYFIC until neurologic toxicity, including ICANS resolves, and modify the next dose or permanently discontinue based on severity [see Dosage and Administration (2.2, 2.4, 2.5) and Warnings and Precautions (5.2)].
- Because of the risk of CRS and neurologic toxicity, including ICANS, LYNOZYFIC is available only through a restricted program under a Risk Evaluation and Mitigation Strategy (REMS) called the LYNOZYFIC REMS [see Warnings and Precautions (5.3)].

1 INDICATIONS AND USAGE

LYNOZYFIC is indicated for the treatment of adult patients with relapsed or refractory multiple myeloma who have received at least four prior lines of therapy, including a proteasome inhibitor, an immunomodulatory agent, and an anti-CD38 monoclonal antibody.

This indication is approved under accelerated approval based on response rate and durability of response [see Clinical Studies (14)]. Continued approval for this indication may be contingent upon verification and description of clinical benefit in confirmatory trial(s).

2 DOSAGE AND ADMINISTRATION

2.1 Important Administration Instructions

- Administer LYNOZYFIC intravenously according to the step-up schedule to reduce the incidence and severity of cytokine release syndrome (CRS) [see Dosage and Administration (2.2)].
- Administer only as an intravenous infusion after dilution in 0.9% Sodium Chloride Injection [see Dosage and Administration (2.6)].
- Administer pretreatment medications [see Dosage and Administration (2.3)].
- LYNOZYFIC should be administered by a healthcare provider with immediate access to emergency equipment and appropriate medical support to manage severe reactions such as cytokine release syndrome (CRS), infusion-related reactions (IRR), and neurologic toxicity, including ICANS [see Warnings and Precautions (5.1 and 5.2)].
- Due to the risk of CRS and neurologic toxicity, including ICANS, patients should be hospitalized for 24 hours after administration of the first step-up dose, and for 24 hours after administration of the second step-up dose.

2.2 Recommended Dosage

The recommended dosage for LYNOZYFIC is presented in Table 1. In patients who experience CRS, ICANS, or neurologic adverse reactions, refer to Tables 3, 4, and 5, respectively, for recommendations regarding administration of the next LYNOZYFIC dose. Continue treatment until disease progression or unacceptable toxicity. The recommended dosing schedule for LYNOZYFIC is provided in Table 1. The recommended dosage of LYNOZYFIC is step-up doses of 5 mg, 25 mg, and 200 mg, followed by 200 mg weekly for 10 doses, followed by 200 mg biweekly (every 2 weeks). In patients who have achieved and maintained VGPR or better at or after Week 24 and received at least 17 doses of 200 mg, decrease the dosing frequency to 200 mg every 4 weeks.

Table 1: LYNOZYFIC Dosing Schedule
Dosing Schedule | Day [Weekly doses should be at least 5 days apart. Biweekly doses should be at least 10 days apart. Every 4-week doses should be at least 24 days apart.] | LYNOZYFIC Dose |  | Duration of Infusion
Step-up Dosing Schedule | Day 1 | Step-up dose 1 | 5 mg | 4 hours
Step-up Dosing Schedule | Day 8 | Step-up dose 2 | 25 mg | 4 hours
Step-up Dosing Schedule | Day 15 | First treatment dose | 200 mg | 4 hours
Weekly Dosing Schedule | One week after Day 15 treatment dose and once weekly from Week 4 to Week 13 for 10 treatment doses | Second and subsequent treatment doses | 200 mg | 1 hour for the second treatment dose, and 30 minutes for subsequent doses [For patients who experienced CRS with the previous dose of LYNOZYFIC, the duration of infusion should be maintained at the duration of the previous infusion; reduce the duration of infusion sequentially in subsequent doses in patients who do not experience CRS (e.g., 4 hours, 1 hour, then 30 minutes).]
Biweekly (Every 2 Weeks) Dosing Schedule | Week 14 and every 2 weeks thereafter | Subsequent treatment doses | 200 mg | 30 minutes
Patients who have achieved and maintained VGPR or better at or after Week 24 and received at least 17 doses of 200 mg
Every 4 Weeks Dosing Schedule | At Week 24 or after and every 4 weeks thereafter |  | 200 mg | 30 minutes

2.3 Recommended Pretreatment Medications

Administer the following pre-treatment medications before each dose of the LYNOZYFIC step-up dosing schedule, which includes step-up dose 1, step-up dose 2, and the first treatment dose, the second treatment dose, and if indicated, subsequent treatment doses (see Tables 1, 2, and 3), to reduce the risk of CRS and/or IRR [see Warnings and Precautions (5.1)]:

- acetaminophen (or equivalent) 650 mg to 1,000 mg orally 30 to 60 minutes prior to infusion
- diphenhydramine (or equivalent) 25 mg orally or intravenously 30 to 60 minutes prior to infusion
- dexamethasone (or equivalent) intravenously 1 to 3 hours prior to infusion
  - 40 mg dexamethasone (or equivalent) before step-up dose 1, step-up dose 2, and the first full treatment dose
  - Once a treatment dose of LYNOZYFIC is tolerated without CRS and/or IRR with 40 mg dexamethasone (or equivalent), administer 10 mg dexamethasone (or equivalent) prior to the subsequent LYNOZYFIC treatment dose

Pre-treatment medications may be discontinued once a treatment dose of LYNOZYFIC is tolerated without CRS and/or IRR following pre-treatment with 10 mg dexamethasone (or equivalent), acetaminophen (or equivalent), and diphenhydramine (or equivalent) as described.

2.4 Restarting LYNOZYFIC After Dosage Delay

Table 2 provides recommendations for restarting therapy after a dose delay. Refer to Table 3, Table 4, and Table 5 for recommendations about management of CRS, ICANS, or other adverse reactions.

Table 2: Recommendations for Restarting Therapy with LYNOZYFIC After a Dose Delay
Last Dose Administered | Time since the last dose administered [Consider benefit-risk of restarting LYNOZYFIC in patients who require a dose delay of more than 30 days.] | Action for next dose. (For CRS/IRR or ICANS, refer to the dose modifications in Table 3, Table 4, and Table 5.)
5 mg | 14 days or less | Administer 25 mg
5 mg | Greater than 14 days | Restart step-up dosing from 5 mg
25 mg | 14 days or less | Administer 200 mg
25 mg | Greater than 14 days and less than or equal to 28 days | Restart step-up dosing from 25 mg
25 mg | Greater than 28 days | Restart step-up dosing from 5 mg
200 mg | 49 days or less | Administer 200 mg
200 mg | Greater than 49 days | Restart step-up dosing from 5 mg
NOTE: Administer pre-treatment medications prior to step-up dose 1, step-up dose 2, the first treatment dose, the second treatment dose, and if indicated, subsequent treatment doses [see Dosage and Administration (2.3)].

2.5 Management of Adverse Reactions

Table 3 describes the management of CRS. Table 4 describes the management of ICANS. Table 5 describes the management of other adverse reactions.

Cytokine Release Syndrome

Identify CRS based on clinical presentation [see Warnings and Precautions (5.1)]. Evaluate and treat other causes of fever, hypoxia, and hypotension. If CRS is suspected, withhold LYNOZYFIC until CRS resolves. CRS should be managed according to the recommendations in Table 3 and per current practice guidelines. Supportive therapy for CRS should be administered, which may include intensive care for severe or life-threatening CRS.

Table 3: Recommendations for Management of Cytokine Release Syndrome
Grade [Based on American Society for Transplantation and Cellular Therapy (ASTCT) criteria for grading CRS (2019).] | Presenting Symptoms | Recommendations
Grade 1 | Fever ≥100.4ºF (38ºC) [Attributed to CRS. Fever may not always be present concurrently with hypotension or hypoxia as it may be masked by interventions such as steroids, antipyretics, or anticytokine therapy.] | - Withhold LYNOZYFIC until CRS resolves. - Provide supportive care, which may include intensive care. - When CRS resolves, resume LYNOZYFIC. [Administer pretreatment medications prior to next dose [see Dosage and Administration (2.3)].] , [Follow the recommendations in Table 2 for restarting dosing.]
Grade 2 | Fever ≥100.4°F (38°C) with: Hypotension responsive to fluids and not requiring vasopressors and/or hypoxia requiring low-flow oxygen [Low-flow oxygen defined as oxygen delivered at less than 6 L/minute: high-flow oxygen defined as oxygen delivered at greater than or equal to 6 L/minute.] by nasal cannula or blow-by | - Withhold LYNOZYFIC until CRS resolves. - Provide supportive care, which may include intensive care. - When CRS resolves, resume treatment with LYNOZYFIC., - Consider a decrease in infusion rate up to 50% (no more than 6 hours total) when resuming treatment. Increase rate on subsequent infusions if tolerated. - Monitor patients within proximity of a healthcare facility for 24 hours following this dose, and consider hospitalization.
Grade 3 | Fever ≥100.4°F (38°C) with: Hypotension requiring a vasopressor (with or without vasopressin) and/or hypoxia requiring high-flow oxygen by nasal cannula, face mask, non-rebreather mask, or Venturi mask. | - Withhold LYNOZYFIC until CRS resolves. - Provide supportive care, which may include intensive care. - When CRS resolves, resume treatment with LYNOZYFIC at reduced dose:, [If the last dose administered was 5 mg, administer 2.5 mg. If the last dose administered was 25 mg, restart step-up dosing from 5 mg. If the last dose administered was 200 mg, refer to Table 2 for recommendations regarding restarting therapy based on time since the last dose.] - Decrease infusion rate up to 50% (no more than 6 hours total). - Hospitalize for 24 hours after the administration for this dose. - After resuming treatment, if the administered dose is tolerated: - Continue with the next dose of the recommended dosing regimen per Table 1. - If the full dose is tolerated, infusion rate can be increased to the rate prior to the adverse reaction. - Permanently discontinue LYNOZYFIC if Grade 3 CRS recurs with subsequent infusions.
Grade 4 | Fever ≥100.4°F (38°C) with: Hypotension requiring multiple vasopressors (excluding vasopressin) and/or hypoxia requiring oxygen by positive pressure (e.g., continuous positive airway pressure (CPAP), bilevel positive airway pressure (BiPAP), intubation, and mechanical ventilation). | - Discontinue LYNOZYFIC permanently. - CRS should be managed per Grade 3 recommendations.
Other | AST/ALT greater than 5 times ULN associated with CRS Grade 3 or less | - Withhold LYNOZYFIC until CRS resolves and AST/ALT are less than 3 times ULN if baseline was normal or 1.5 to 3 times baseline if baseline was abnormal. - Provide supportive care, which may include intensive care, and monitor. - No change in dose is needed in patients without CRS symptoms with transaminase levels that are trending towards baseline within 7 days. - If values do not trend towards baseline in 7 days, decrease the dose. - See infusion rate information by CRS grade.

Neurologic Toxicity, including ICANS

Management recommendations for ICANS and neurologic toxicity are summarized in Table 4 and Table 5. At the first sign of suspected neurologic toxicity, including ICANS, withhold LYNOZYFIC and consider consultation with neurologist and other specialists for further evaluation and management. Rule out other causes of neurologic symptoms. Provide supportive therapy, which may include intensive care for severe or life-threatening ICANS. Manage per current practice guidelines.

Table 4: Recommendations for Management of ICANS
Grade [Based on American Society for Transplantation and Cellular Therapy (ASTCT) 2019 grading for ICANS.] | Presenting Symptoms [Management is determined by the most severe event, not attributable to any other cause.] | Recommendations
Grade 1 | ICE [If patient is arousable and able to perform Immune Effector Cell-Associated Encephalopathy (ICE) Assessment, assess: Orientation (oriented to year, month, city, hospital=4 points); Naming (name 3 objects, e.g., point to clock, pen, button=3 points); Following Commands (e.g., "show me 2 fingers" or "close your eyes and stick out your tongue"=1 point); Writing (ability to write a standard sentence=1 point); and Attention (count backwards from 100 by ten=1 point). If patient is unarousable and unable to perform ICE Assessment (Grade 4 ICANS)=0 points.] score 7-9, or depressed level of consciousness [Not attributable to any other cause.] : awakens spontaneously. | - Withhold until neurologic symptoms resolve or return to baseline. [Follow the recommendations in Table 2 for restarting dosing.] - Provide supportive therapy. Manage per current practice guidelines. - Consider non-sedating, anti-seizure medications for seizure prophylaxis.
Grade 2 | ICE score 3-6, or depressed level of consciousness: awakens to voice. | - Withhold until neurologic symptoms resolve or return to baseline. - Provide supportive therapy. Manage per current practice guidelines. - Administer dexamethasone [All references to dexamethasone administration are dexamethasone or equivalent.] 10 mg intravenously every 6 hours. Continue dexamethasone use until resolution to Grade 1 or less, then taper. - Consider non-sedating, anti-seizure medications for seizure prophylaxis. - Monitor patients within proximity of a healthcare facility for 24 hours following the next dose of LYNOZYFIC and consider hospitalization.
Grade 3 | ICE score 0-2, or depressed level of consciousness: awakens only to tactile stimulus, or seizures, either:; - any clinical seizure, focal or generalized, that resolves rapidly, or - non-convulsive seizures on electroencephalogram (EEG) that resolve with intervention,; or raised intracranial pressure: focal/local edema on neuroimaging. | - Withhold until neurologic symptoms resolve or return to baseline. - Provide supportive therapy, which may include intensive care. Manage per current practice guidelines. - Consider neurology evaluation. - Administer dexamethasone 10 mg intravenously every 6 hours. Continue dexamethasone use until resolution to Grade 1 or less, then taper. - Consider non-sedating, anti-seizure medications for seizure prophylaxis. - Permanently discontinue LYNOZYFIC for recurrent Grade 3 ICANS. - Resume treatment with LYNOZYFIC at a reduced dose [If the last dose administered was 5 mg, administer 2.5 mg. If the last dose administered was 25 mg, restart step-up dosing from 5 mg. If the last dose administered was 200 mg, refer to Table 2 for recommendations regarding restarting therapy based on time since the last dose.] and hospitalize for 24 hours after the administration of the dose. After resuming treatment, if the administered dose is tolerated, continue with the next dose of the recommended dosing regimen per Table 1.
Grade 4 | ICE score 0, or depressed level of consciousness: either:; - patient is unarousable or requires vigorous or repetitive tactile stimuli to arouse, or - stupor or coma,; or seizures, either:; - life-threatening prolonged seizure (>5 minutes), or - repetitive clinical or electrical seizures without return to baseline in between,; or motor findings:; - deep focal motor weakness such as hemiparesis or paraparesis,; or raised intracranial pressure/cerebral edema, with signs/ symptoms such as:; - diffuse cerebral edema on neuroimaging, or - decerebrate or decorticate posturing, or - cranial nerve VI palsy, or - papilledema, or - Cushing's triad. | - Permanently discontinue LYNOZYFIC. - Provide supportive therapy, which may include intensive care. Manage per current practice guidelines. - Consider neurology evaluation. - Administer dexamethasone 10 mg intravenously every 6 hours. Continue dexamethasone use until resolution to Grade 1 or less, then taper. - Consider non-sedating, anti-seizure medications for seizure prophylaxis.

Other Adverse Reactions

Management recommendations for other adverse reactions are summarized in Table 5.

Table 5: Recommendations for Management of Other Adverse Reactions
Adverse Reaction | Severity [Based on National Cancer Institute Common Terminology Criteria for Adverse Events (NCI-CTCAE), Version 5.0] | Recommendations
Infusion-Related Reactions | Grade 2 | - Stop infusion and treat symptoms. - May resume treatment with the remaining infusion (total infusion time must not exceed 6 hours total) when symptoms are Grade 1 or baseline. - Consider decreasing infusion rate by up to 50% when resuming treatment. If tolerated, infusion rate can be increased with subsequent doses.
Infusion-Related Reactions | Grade 3 | - Stop infusion and treat symptoms. - May resume when symptoms are Grade 1 or baseline. - After resolution of the adverse event, follow the recommendations: - Decrease the infusion rate up to 50% (no more than 6 hours total). - Resume at reduced dose. [If the last dose administered was 5 mg, administer 2.5 mg. If the last dose administered was 25 mg, restart step-up dosing from 5 mg. If the last dose administered was 200 mg, refer to Table 2 for recommendations regarding restarting therapy based on time since the last dose.] - If the administered dose is tolerated, continue with the next dose of the recommended dosing regimen at the decreased infusion rate. - Infusion rate can be increased if tolerated. - Permanently discontinue LYNOZYFIC if Grade 3 IRR recurs with subsequent infusions.
Infusion-Related Reactions | Grade 4 | - Permanently discontinue LYNOZYFIC and treat symptoms.
Neurologic Adverse Reactions (excluding ICANS) | Grade 2 | - Withhold LYNOZYFIC until symptoms resolve to Grade 1 or baseline. [Follow the recommendations in Table 2 for restarting dosing.]
Neurologic Adverse Reactions (excluding ICANS) | Grade 3 (First occurrence) | - Withhold LYNOZYFIC until Grade 1 or baseline.
Neurologic Adverse Reactions (excluding ICANS) | Grade 3 (Recurrent) Grade 4 | - Permanently discontinue LYNOZYFIC.
Infections | Grades 2 or 3 | - Withhold LYNOZYFIC in patients with active infection until the infection improves to Grade 1 or less.
Infections | Grade 4 | - Consider permanent discontinuation of LYNOZYFIC. If treatment is not permanently discontinued, withhold subsequent treatment doses until Grade 1 or baseline.
Other Non-hematologic Adverse Reactions | Grade 3 | - Withhold LYNOZYFIC until Grade 1 or baseline.
Other Non-hematologic Adverse Reactions | Grade 4 | - Consider permanent discontinuation of LYNOZYFIC. - If LYNOZYFIC is not permanently discontinued, withhold subsequent treatment doses until Grade 1 or baseline.
Hematologic Adverse Reactions | Platelet count less than 50,000/mcL with bleeding OR less than 25,000/mcL | - Withhold LYNOZYFIC until 25,000/mcL or higher and no evidence of bleeding.
Hematologic Adverse Reactions | Absolute neutrophil count less than 1 × 10^9/L with Grade 2 or higher infection OR less than 0.5 × 10^9/L | - Withhold LYNOZYFIC until 0.5 × 10^9/L or higher.
Hematologic Adverse Reactions | Febrile neutropenia | - Withhold LYNOZYFIC until neutrophil count is greater than 1 × 10^9/L and fever resolves.
Hematologic Adverse Reactions | Hemoglobin less than 8 g/dL | - Withhold LYNOZYFIC until hemoglobin is 8 g/dL or higher.

2.6 Preparation and Administration

Preparation

- Use aseptic technique to prepare LYNOZYFIC. Each vial is intended for one time use only. Do not shake.
- Parenteral drug products should be inspected visually for particulate matter and discoloration prior to administration, whenever solution and container permit. LYNOZYFIC is a clear to slightly opalescent, colorless to pale yellow solution. Discard the vial if the solution is cloudy, discolored, or contains particulate matter.
- Determine the dose, total volume of LYNOZYFIC solution, and the number of LYNOZYFIC vials needed (see Table 6).

Dilution

- Withdraw the desired dose from the vial of LYNOZYFIC and transfer into an intravenous infusion bag [polyvinyl chloride (PVC) or polyolefin (PO)] of 0.9% Sodium Chloride Injection, according to Table 6. Discard any unused portion left in the vial.
- Mix diluted solution by gentle inversion. Do not shake the solution.

Table 6: Dilution of LYNOZYFIC
LYNOZYFIC dose | LYNOZYFIC vial strength | Volume of LYNOZYFIC to be added to the infusion bag | Size of 0.9% Sodium Chloride Injection Infusion Bag (PVC or PO)
2.5 mg [Modified dose due to adverse reaction. For instructions on when to use the modified dose refer to Table 3, Table 4, and Table 5.] | 5 mg/2.5 mL | 1.25 mL | 50 mL
5 mg | 5 mg/2.5 mL | 2.5 mL | 50 mL or 100 mL
25 mg | 5 mg/2.5 mL | 12.5 mL | 50 mL or 100 mL
200 mg | 200 mg/10 mL | 10 mL | 50 mL or 100 mL

Diluted LYNOZYFIC Storage

Use diluted LYNOZYFIC immediately. If not used immediately, store the solution:

- at room temperature up to 25°C (77°F) for no more than 8 hours from preparation to the start of the infusion.
  Or
- under refrigeration at 2°C to 8°C (36°F to 46°F) for no more than 48 hours from preparation to the start of the infusion.

Do not freeze.

Do not shake.

Administration

- Administer as an intravenous infusion only.
- Refer to Dosage and Administration (2.2) for infusion rates.
- Connect the prepared intravenous infusion bag containing the final LYNOZYFIC solution to intravenous tubing constructed of PVC, polyethylene (PE)-lined PVC, or polyurethane (PU).
- Use of a 0.2-micron to 5-micron polyethersulfone (PES) filter is required.
- Prime with LYNOZYFIC to the end of the intravenous tubing.
- Do not mix LYNOZYFIC with other drugs or concurrently administer other drugs through the same intravenous line.
- Upon completion of LYNOZYFIC infusion, flush the infusion line with an adequate volume of sterile 0.9% Sodium Chloride Injection to ensure that the entire contents of the infusion bag are administered.
- Total infusion time should include flushing of the infusion line.

3 DOSAGE FORMS AND STRENGTHS

LYNOZYFIC is a clear to slightly opalescent, colorless to pale yellow solution, available as:

- Injection: 5 mg/2.5 mL (2 mg/mL) single-dose vial
- Injection: 200 mg/10 mL (20 mg/mL) single-dose vial

4 CONTRAINDICATIONS

None.

5 WARNINGS AND PRECAUTIONS

5.1 Cytokine Release Syndrome (CRS)

LYNOZYFIC can cause cytokine release syndrome (CRS), which can be serious or life-threatening.

In LINKER-MM1, CRS occurred in 46% (54/117) of patients who received LYNOZYFIC at the recommended dose, with Grade 1 CRS occurring in 35% (41/117) of patients, Grade 2 in 10% (12/117), and Grade 3 in 0.9% (1/117) [see Adverse Reactions (6.1)]. Thirty-eight percent (45/117) of patients had CRS following step-up dose 1, including 1 patient who experienced Grade 3 CRS; 8% (9/117) had an initial CRS event following a subsequent dose. Seventeen percent (19/113) of patients developed CRS after step-up dose 2, 10% (11/111) developed CRS after the first full 200 mg dose of LYNOZYFIC, and 3.6% (4/110) developed CRS after the second full dose. Recurrent CRS occurred in 20% (23/117) of patients. The median time to onset of CRS from the end of infusion was 11 (range: -1 to 184) hours after the most recent dose with a median duration of 15 (range: 1 to 76) hours.

Clinical signs and symptoms of CRS included, but were not limited to pyrexia, chills, hypoxia, tachycardia, and hypotension.

Administer pretreatment medications and initiate therapy according to LYNOZYFIC step-up dosing to reduce the incidence and severity of CRS [see Dosage and Administration (2.2) and Dosage and Administration (2.3)].

Monitor patients for signs and symptoms of CRS after infusion. Counsel patients to seek immediate medical attention should signs or symptoms of CRS occur.

At the first sign of CRS, immediately evaluate patients for hospitalization, manage per current practice guidelines, and administer supportive care; withhold LYNOZYFIC until CRS resolves and modify the next dose or permanently discontinue LYNOZYFIC based on severity [see Dosage and Administration (2.5)].

Infusion Related Reactions

Infusion-related reactions (IRR) may be clinically indistinguishable from manifestations of CRS. In the patients who were treated with the recommended step-up dosing regimen and pretreatment medications [see Dosage and Administration (2.2) and Dosage and Administration (2.3)], the rate of IRR was 9% [11/117 including Grade 2 IRR (4.3%) and Grade 3 IRR (1.7%)]. For IRR, interrupt or slow the rate of infusion or permanently discontinue LYNOZYFIC based on severity of reaction [see Dosage and Administration (2.5)].

LYNOZYFIC is available only through a restricted program under a REMS [see Warnings and Precautions (5.3)].

5.2 Neurologic Toxicity, including Immune Effector Cell-Associated Neurotoxicity Syndrome

LYNOZYFIC can cause serious or life-threatening neurologic toxicity, including immune effector cell-associated neurotoxicity syndrome (ICANS) [see Adverse Reactions (6.1)].

In LINKER-MM1, neurologic toxicity occurred in 54% of patients, with Grade 3 or 4 neurologic toxicity occurring in 8%, at the recommended dose [see Adverse Reactions (6.1)]. Neurologic toxicities included ICANS, depressed level of consciousness, encephalopathy, and toxic encephalopathy.

ICANS occurred in 8% of patients who received LYNOZYFIC with the recommended dosing regimen, including Grade 3 events in 2.6%. Most patients experienced ICANS following step-up dose 1 (5%). Two patients (1.8%) experienced initial ICANS following step-up dose 2 and one patient developed the first occurrence of ICANS following a subsequent full dose of LYNOZYFIC. Recurrent ICANS occurred in one patient. The median time to onset of ICANS was 1 (range: 1 to 4) day after the most recent dose with a median duration of 2 (range: 1 to 11) days. The onset of ICANS can be concurrent with CRS, following resolution of CRS, or in the absence of CRS.

The most common clinical signs and symptoms of ICANS are confusion, depressed level of consciousness, and lethargy. Monitor patients for signs and symptoms of neurologic toxicity during treatment. At the first sign of neurologic toxicity, including ICANS, immediately evaluate the patient; provide supportive therapy and consider further management per current practice guidelines. Withhold LYNOZYFIC until ICANS resolves and modify the next dose or permanently discontinue LYNOZYFIC based on severity [see Dosage and Administration (2.5)]. Counsel patients to seek immediate medical attention should signs or symptoms of neurologic toxicity occur at any time.

Due to the potential for neurologic toxicity, including ICANS, patients receiving LYNOZYFIC are at risk of confusion and depressed consciousness. Advise patients to refrain from driving, or operating heavy or potentially dangerous machinery, for 48 hours after completion of each of the step-up doses [see Dosage and Administration (2.2)] and in the event of new onset of any neurological symptoms, until symptoms resolve.

LYNOZYFIC is available only through a restricted program under a REMS [see Warnings and Precautions (5.3)].

5.3 LYNOZYFIC REMS

LYNOZYFIC is available only through a restricted program under a REMS called the LYNOZYFIC REMS because of the risks of CRS and neurologic toxicity, including ICANS [see Warnings and Precautions (5.1, 5.2)].

Notable requirements of the LYNOZYFIC REMS include the following:

- Prescribers must be certified with the program by enrolling and completing training.
- Prescribers must counsel patients receiving LYNOZYFIC about the risk of CRS and neurologic toxicity, including ICANS, and provide patients with LYNOZYFIC Patient Wallet Card.
- Pharmacies and healthcare settings that dispense LYNOZYFIC must be certified with the LYNOZYFIC REMS program and must verify prescribers are certified through the LYNOZYFIC REMS program.
- Wholesalers and distributors must only distribute LYNOZYFIC to certified pharmacies or healthcare settings.

Further information about the LYNOZYFIC REMS program is available at lynozyficREMS.com or by telephone at 1-855-212-6391.

5.4 Infections

LYNOZYFIC can cause serious, life-threatening, or fatal infections.

In patients who received LYNOZYFIC at the recommended dose in LINKER-MM1, serious infections, including opportunistic infections, occurred in 42% of patients, with Grade 3 or 4 infections in 38% and fatal infections in 4% [see Adverse Reactions (6.1)]. The most common serious infection reported (≥10%) were pneumonia and sepsis. Two cases of progressive multifocal leukoencephalopathy (PML) occurred in patients receiving LYNOZYFIC.

Monitor patients for signs and symptoms of infection and immunoglobulin levels prior to and during treatment with LYNOZYFIC and treat appropriately. Administer prophylactic antimicrobials, antibiotics, antifungals, antivirals, vaccines, and subcutaneous or intravenous immunoglobulin (IVIG) according to guidelines, including prophylaxis for PJP and herpesviruses [see Dosage and Administration (2.3)].

Withhold LYNOZYFIC or consider permanent discontinuation of LYNOZYFIC based on severity of the infection [see Dosage and Administration (2.5)].

5.5 Neutropenia

LYNOZYFIC can cause neutropenia and febrile neutropenia.

In patients who received LYNOZYFIC at the recommended dose in LINKER-MM1, decreased neutrophil count occurred in 62% of patients with Grade 3 or 4 decreased neutrophil count in 47%. Febrile neutropenia occurred in 8% of patients [see Adverse Reactions (6.1)].

Monitor complete blood cell counts at baseline and periodically during treatment and provide supportive care per local guidelines. Monitor patients with neutropenia for signs of infection. Withhold LYNOZYFIC based on severity [see Dosage and Administration (2.5)].

5.6 Hepatotoxicity

LYNOZYFIC can cause hepatotoxicity.

In LINKER-MM1, elevated ALT occurred in 46% of patients, with Grade 3 or 4 ALT elevation occurring in 6%; elevated AST occurred in 61% of patients, with Grade 3 or 4 AST elevation occurring in 10% of patients who received the recommended dose. Grade 3 or 4 total bilirubin elevations occurred in 1.7% of patients [see Adverse Reactions (6.1)]. Liver enzyme elevation can occur with or without concurrent CRS.

Monitor liver enzymes and bilirubin at baseline and during treatment as clinically indicated. Withhold LYNOZYFIC or consider permanent discontinuation of LYNOZYFIC based on severity [see Dosage and Administration (2.5)].

5.7 Embryo-Fetal Toxicity

Based on its mechanism of action, LYNOZYFIC may cause fetal harm when administered to a pregnant woman. Advise pregnant women of the potential risk to the fetus. Advise females of reproductive potential to use effective contraception during treatment with LYNOZYFIC and for 3 months after the last dose [see Use in Specific Populations (8.1, 8.3)].

6 ADVERSE REACTIONS

The following clinically significant adverse reactions are described elsewhere in the labeling:

- Cytokine Release Syndrome [see Warnings and Precautions (5.1)]
- Neurologic Toxicity, including Immune Effector Cell-Associated Neurotoxicity Syndrome [see Warnings and Precautions (5.2)]
- Infections [see Warnings and Precautions (5.4)]
- Neutropenia [see Warnings and Precautions (5.5)]
- Hepatotoxicity [see Warnings and Precautions (5.6)]

6.1 Clinical Trials Experience

Because clinical trials are conducted under widely varying conditions, adverse reaction rates observed in the clinical trials of a drug cannot be directly compared to rates in the clinical trials of another drug and may not reflect the rates observed in practice.

Relapsed or Refractory Multiple Myeloma

The safety of LYNOZYFIC was evaluated in LINKER-MM1 [see Clinical Studies (14)]. Patients (n=117) received LYNOZYFIC as step-up doses of 5 mg on Day 1 and 25 mg on Day 8, and the first treatment dose of 200 mg on Day 15. Patients then received 200 mg intravenously once weekly from Week 4 to Week 13, followed by 200 mg every 2 weeks from Week 14. In the Phase 2 portion of the study, patients who achieved and maintained VGPR or better at or after Week 24 and received at least 17 doses of 200 mg were able to receive every 4-week dosing. The median duration of treatment was 47 weeks (range 1, 151); 55% of patients were exposed for 9 months or longer and 36% were exposed for 1 year or longer.

The median age of patients who received LYNOZYFIC was 70 years (range: 37 to 91 years); 55% were male; 71% were White, 17% were Black or African American, and 9% were Asian.

Serious adverse reactions occurred in 74% of patients who received LYNOZYFIC. Serious adverse reactions that occurred in >5% of patients included cytokine release syndrome (27%), pneumonia (13%), COVID-19 (7%), and acute kidney injury (5%). Fatal adverse reactions occurred in 7% of patients, and included sepsis (3.4%), chronic kidney disease (0.9%), pneumonia (0.9%), tumor lysis syndrome (0.9%), and encephalopathy (0.9%).

Permanent discontinuation of LYNOZYFIC due to adverse reactions occurred in 16% of patients. Adverse reactions leading to discontinuation that occurred in at least 2 patients included sepsis, pneumonia, and encephalopathy.

Dosage interruptions or delays of LYNOZYFIC due to adverse reactions occurred in 74% of patients. Adverse reactions which required a dosage interruption or delay in >10% of patients included neutropenia (29%), upper respiratory tract infection (18%), pneumonia (15%), and COVID-19 infection (11%).

The most common adverse reactions (≥20%) were musculoskeletal pain, cytokine release syndrome, cough, upper respiratory tract infection, diarrhea, fatigue, pneumonia, nausea, headache, and dyspnea. The most common Grade 3 to 4 laboratory abnormalities (≥30%) were decreased lymphocyte count, decreased neutrophil count, decreased hemoglobin, and decreased white blood cell count.

Table 7 summarizes the adverse reactions in LINKER-MM1.

Table 7: Adverse Reactions (≥10%) in Patients with Relapsed or Refractory Multiple Myeloma Who Received LYNOZYFIC in LINKER-MM1
Adverse Reaction | LYNOZYFIC (N=117)
Adverse Reaction | All Grades (%) | Grade 3 or 4 (%)
Musculoskeletal and connective tissue disorders
Musculoskeletal pain [Includes other related terms.] | 53 | 3.4 [Only Grade 3 adverse reactions occurred.]
Immune system disorders
Cytokine release syndrome | 46 | 0.9
Hypogammaglobulinemia | 13 | 0.9
Respiratory, thoracic and mediastinal disorders
Cough | 39 | 0
Dyspnea | 21 | 0.9
Nasal congestion | 16 | 0
Infections and infestations
Upper respiratory tract infection | 35 | 6
Pneumonia [Pneumonia includes atypical pneumonia, COVID-19 pneumonia, PJP, pneumonia, pneumonia cytomegaloviral, pneumonia fungal, pneumonia influenzal, and pneumonia viral.] , [Includes fatal outcome.] | 28 | 21
COVID-19 | 17 | 5
Urinary tract infections | 16 | 8
Sepsis | 10 | 6
Gastrointestinal disorders
Diarrhea | 35 | 1.7
Nausea | 23 | 0
Vomiting | 19 | 0
Constipation | 17 | 0
General disorders and administration site conditions
Fatigue | 34 | 0
Edema | 19 | 0.9
Pyrexia | 17 | 0
Nervous system disorders
Headache | 22 | 0.9
Encephalopathy, [Encephalopathy includes agitation, amnesia, cognitive disorder, confusional state, delirium, depressed level of consciousness, encephalopathy (including hyperammonemic and toxic encephalopathy), irritability, lethargy, memory impairment, mental status changes, somnolence, and excludes ICANS.] | 18 | 3.4
Sensory Neuropathy | 13 | 0.9
Metabolism and nutrition disorders
Decreased appetite | 15 | 0.9
Skin and subcutaneous tissue disorders
Rash [Rash includes dermatitis acneiform, dermatitis contact, drug eruption, erythema, rash, rash erythematous, rash maculo-papular, rash pruritic, and stasis dermatitis.] | 15 | 1.7
Psychiatric disorders
Insomnia | 13 | 0
Vascular disorders
Hypertension | 10 | 4.3

Clinically significant adverse reactions that occurred in <10% of patients treated with LYNOZYFIC included IRR, motor dysfunction, febrile neutropenia, ICANS, CMV infection, and PML.

Table 8 summarizes the laboratory abnormalities in LINKER-MM1.

Table 8: Select Laboratory Abnormalities (≥5% for Grade 3 or 4) That Worsened from Baseline in Patients with Multiple Myeloma Treated with LYNOZYFIC in LINKER-MM1
Laboratory Abnormality [Laboratory tests were graded according to NCI-CTCAE (National Cancer Institute Common Terminology Criteria for Adverse Events) Version 5.0.] | LYNOZYFIC (N=117) [The denominator used to calculate the rate varied from 106 to 117 based on the number of patients with a baseline value and at least one post-treatment value.]
 | All Grades (%) | Grades 3 or 4 (%)
Hematology
Lymphocyte count decreased | 97 | 92
Hemoglobin decreased | 72 | 42
Platelet count decreased | 64 | 19
White blood cell count decreased | 63 | 31
Neutrophil count decreased | 62 | 47
Chemistry
Aspartate aminotransferase increased | 61 | 10
Phosphorus decreased | 55 | 24
Creatinine increased | 47 | 7
Alanine aminotransferase increased | 46 | 6

7 DRUG INTERACTIONS

7.1 Effects of LYNOZYFIC on Other Drugs

Certain CYP substrates

Monitor for toxicity unless otherwise recommended in the Prescribing Information of certain CYP substrates where minimal changes in the concentration may lead to serious adverse reactions when used concomitantly with LYNOZYFIC.

Linvoseltamab-gcpt causes the release of cytokines [see Clinical Pharmacology (12.2)] that may suppress cytochrome P450 (CYP) enzyme activity. Concomitant use with LYNOZYFIC increases CYP substrate exposure which may increase the risk of adverse reactions related to these substrates. Increased CYP substrate exposure is more likely to occur from initiation of the LYNOZYFIC step-up dosing schedule up to 14 days after the first 200 mg dose, and during and after CRS [see Warnings and Precautions (5.1)].

8 USE IN SPECIFIC POPULATIONS

8.1 Pregnancy

Risk Summary

Based on the mechanism of action, LYNOZYFIC may cause fetal harm when administered to a pregnant woman [see Clinical Pharmacology (12.1)]. There are no available data on the use of LYNOZYFIC in pregnant women to evaluate for a drug associated risk. No animal reproductive or developmental toxicity studies have been conducted with LYNOZYFIC.

Linvoseltamab-gcpt causes T-cell activation and cytokine release; immune activation may compromise pregnancy maintenance. In addition, based on the finding of B-cell depletion in non-pregnant animals, linvoseltamab-gcpt can cause B-cell lymphocytopenia in infants exposed to linvoseltamab-gcpt in-utero. Human immunoglobulin (IgG) is known to cross the placenta after the first trimester of pregnancy; therefore, linvoseltamab-gcpt has the potential to be transmitted from the mother to the developing fetus. Advise women of the potential risk to the fetus.

LYNOZYFIC is associated with hypogammaglobulinemia, therefore, assessment of immunoglobulin levels in newborns of mothers treated with LYNOZYFIC should be considered.

In the U.S. general population, the estimated background risk of major birth defects and miscarriage in clinically recognized pregnancies is 2% to 4% and 15% to 20%, respectively.

8.2 Lactation

Risk Summary

There are no data on the presence of linvoseltamab-gcpt in human milk, the effects on the breastfed child, or the effects on milk production. Maternal IgG is known to be present in human milk.

Because of the potential for serious adverse reactions in a breastfed child, advise women not to breastfeed during treatment with LYNOZYFIC and for 3 months after the last dose.

8.3 Females and Males of Reproductive Potential

LYNOZYFIC may cause fetal harm when administered to a pregnant woman [see Use in Specific Populations (8.1)].

Pregnancy Testing

Verify the pregnancy status of females of reproductive potential prior to initiating treatment with LYNOZYFIC.

Contraception

Females

Advise females of reproductive potential to use effective contraception during treatment and for 3 months after the last dose of LYNOZYFIC.

8.4 Pediatric Use

The safety and effectiveness of LYNOZYFIC have not been established in pediatric patients.

8.5 Geriatric Use

Of the 117 patients with relapsed or refractory multiple myeloma who received LYNOZYFIC, 42 (36%) of patients were 65 to 74 years of age and 31 (26%) were 75 years of age and older [see Clinical Studies (14)]. No overall differences in safety or effectiveness were observed in patients 65 years of age and older, including patients 75 years of age and older, when compared with younger patients.

11 DESCRIPTION

Linvoseltamab-gcpt, a bispecific B-cell maturation antigen (BCMA)-directed CD3 T-cell engager, is a recombinant human immunoglobulin (Ig)G4 antibody. Linvoseltamab-gcpt is produced by recombinant DNA technology in Chinese hamster ovary (CHO) cell suspension culture. The molecular weight of linvoseltamab-gcpt is approximately 146 kDa.

LYNOZYFIC (linvoseltamab-gcpt) injection for intravenous use is a sterile, preservative-free, clear to slightly opalescent, colorless to pale yellow solution with a pH 6.0.

Each LYNOZYFIC 5 mg/2.5 mL vial contains 5 mg of linvoseltamab-gcpt. Each mL contains 2 mg of linvoseltamab-gcpt, histidine (0.7 mg), L-histidine hydrochloride monohydrate (1.1 mg), polysorbate 80 (1 mg), sucrose (100 mg), and Water for Injection, USP.

Each LYNOZYFIC 200 mg/10 mL vial contains 200 mg of linvoseltamab-gcpt. Each mL contains 20 mg of linvoseltamab-gcpt, histidine (0.7 mg), L-histidine hydrochloride monohydrate (1.1 mg), polysorbate 80 (1 mg), sucrose (100 mg), and Water for Injection, USP.

12 CLINICAL PHARMACOLOGY

12.1 Mechanism of Action

Linvoseltamab-gcpt is a bispecific T-cell engaging antibody that binds to the CD3 receptor expressed on the surface of T-cells and B-cell maturation antigen (BCMA) expressed on the surface of multiple myeloma cells and some healthy B-lineage cells.

In vitro, linvoseltamab-gcpt activated T-cells, caused the release of various proinflammatory cytokines, and resulted in the lysis of multiple myeloma cells. Linvoseltamab-gcpt had anti-tumor activity in mouse models of multiple myeloma.

12.2 Pharmacodynamics

The 200 mg once weekly dosing regimen was associated with better objective response rate and complete response rate when compared to the 50 mg once weekly (0.25 times the recommended dosage) dosing regimen in patients with relapsed or refractory multiple myeloma.

Linvoseltamab-gcpt exposure-response relationships have not been fully characterized.

Effect on Circulating Cytokines

Transient elevation of circulating cytokines (IL-2, IL-6, and IFN-γ) was primarily observed during the step-up dose regimen and the first full 200 mg dose. The highest elevation of cytokines was generally observed 4 hours after each infusion and generally returned to baseline prior to the next dose. Limited cytokine release was observed following subsequent doses.

12.3 Pharmacokinetics

Pharmacokinetic (PK) parameters were evaluated at the recommended dosage in patients with relapsed or refractory multiple myeloma and are presented as geometric mean (CV%) unless otherwise specified.

Linvoseltamab-gcpt PK exposures following use of the recommended dosing schedule are presented in Table 9. Linvoseltamab-gcpt Ctrough increased more than proportionally over a dose range of 96 mg to 800 mg (0.48 to 4 times the recommended full dose). Linvoseltamab-gcpt maximum concentration (127 mg/L [51%]) is achieved after the first dose of the every-2-weeks dosing regimen (i.e., the 12th dose of 200 mg).

Table 9: Geometric Mean (CV%) Exposure Following the Recommended Dosage for Linvoseltamab-gcpt
Dosing Period | Cmax (mg/L) | Ctrough (mg/L) | Cavg (mg /L)
First 200 mg weekly dose | 52.7 (37.2) | 15.5 (64.8) | 27.4 (34.2)
End of 200 mg weekly dosing (11th dose of 200 mg) | 124 (50.4) | 61.8 (123) | 84.6 (74.6)
End of 200 mg every 2 weeks dosing (16th dose of 200 mg) | 97.9 (52.7) | 30.2 (213) | 51.9 (95.3)
Steady state [Steady state values are approximated at Week 28.] with 200 mg every 4 weeks dosing | 64.8 (45.1) | 6.3 (362) | 20.5 (84.6)

Distribution

Linvoseltamab-gcpt volume of distribution (Vd) is 7.05 L (33.6%).

Elimination

Linvoseltamab-gcpt clearance is 0.68 L/day (52.2%) at baseline and 0.43 L/day (83.8%) at steady state.

Linvoseltamab-gcpt clearance decreases over time because its elimination is mediated by two parallel processes: a linear, non-saturable catabolic process and a nonlinear, saturable target-mediated pathway. Patients who discontinue linvoseltamab-gcpt are expected to have a 97% reduction from Cmax at a median (5th to 95th percentile) time of 77.7 (18 to 154) days after last dose.

Metabolism

Linvoseltamab-gcpt is expected to be metabolized into small peptides by catabolic pathways.

Specific Populations

No clinically significant differences in the pharmacokinetics of linvoseltamab-gcpt were observed based on age (37 to 91 years), weight (44 to 172 kg), sex, race (White, Asian, or Black), ethnicity (Hispanic/Latino or not Hispanic/Latino), mild to moderate renal impairment (creatinine clearance [CrCL] 30 to 89 mL/min, by Cockcroft-Gault [C-G] equation), or mild hepatic impairment (total bilirubin less than or equal to upper limit of normal [ULN] with AST greater than ULN or total bilirubin greater than 1 to 1.5 times ULN with any AST).

The effect of severe renal impairment (CrCL 15 to 29 mL/min), end-stage renal disease (CrCL less than 15 mL/min), and moderate to severe hepatic impairment (total bilirubin greater than 1.5 times ULN with any AST) on the pharmacokinetics of linvoseltamab-gcpt is unknown.

12.6 Immunogenicity

The observed incidence of anti-drug antibodies is highly dependent on the sensitivity and specificity of the assay. Differences in assay methods preclude meaningful comparisons of the incidence of anti-drug antibodies in the study described below with the incidence of anti-drug antibodies in other studies, including those of linvoseltamab-gcpt.

During treatment in LINKER-MM1 (evaluated through 30 months) [see Clinical Studies (14)], 1% (2/192) of LYNOZYFIC-treated patients developed anti-linvoseltamab-gcpt antibodies. Because of the low occurrence of anti-drug antibodies, the effect of these antibodies on the pharmacokinetics, pharmacodynamics, safety, and/or effectiveness of linvoseltamab products is unknown.

13 NONCLINICAL TOXICOLOGY

13.1 Carcinogenesis, Mutagenesis, Impairment of Fertility

No carcinogenicity or genotoxicity studies have been conducted with linvoseltamab-gcpt.

No animal studies have been performed to evaluate the effects of linvoseltamab-gcpt on fertility.

14 CLINICAL STUDIES

14.1 Relapsed or Refractory Multiple Myeloma

The efficacy of LYNOZYFIC was evaluated in patients with relapsed or refractory multiple myeloma in an open-label, multi-center, multi-cohort study: LINKER-MM1 (NCT03761108). The study included patients who had previously received at least 3 prior therapies, including a proteasome inhibitor (PI), an immunomodulatory agent (IMiD), and an anti-CD38 antibody. The study included patients with Eastern Cooperative Oncology Group (ECOG) score of 0 or 1 and adequate baseline hematologic (absolute neutrophil count > 1 × 10^9/L, platelet count > 50 × 10^9/L, hemoglobin level >8 g/dL), renal (CrCL > 30 mL/min), and hepatic (AST and ALT ≤ 2.5 × ULN, total bilirubin ≤ 1.5 × ULN, alkaline phosphatase ≤ 2.5 × ULN) function.

The study excluded patients with known multiple myeloma brain lesions or meningeal involvement, history of a neurodegenerative condition, history of seizure within 12 months prior to study enrollment, active infection, a history of an allogeneic or autologous stem cell transplantation within 12 weeks, prior BCMA-directed bispecific antibody therapy, prior bispecific T-cell engaging therapy, or prior BCMA CAR-T cell therapy.

Patients received a step-up dose of 5 mg on Day 1, 25 mg on Day 8, and the first treatment dose of 200 mg on Day 15 of LYNOZYFIC by intravenous infusion. Then, patients received 200 mg of LYNOZYFIC weekly from Week 4 to Week 13, followed by 200 mg every other week thereafter. After at least 24 weeks, the Phase 2 patients who achieved a very good partial response (VGPR) or greater received 200 mg of LYNOZYFIC every 4 weeks. Patients were treated until disease progression or unacceptable toxicity.

The efficacy population included 80 patients who had received at least four prior lines of therapy. The median age was 71 (range: 37 to 83) years with 30% of patients 75 years or older; 64% were male and 36% were female; 69% were White, 14% were Black or African American, 13% were Asian, and 2.5% were Hispanic/Latino.

The International Staging System (ISS) at study entry was Stage I in 39%, Stage II in 36%, and Stage III in 19%. High-risk cytogenetics (presence of del(17p), t(4;14) and t(14;16)) were present in 40% of patients. Eighteen percent of patients had extramedullary disease at baseline.

The median number of prior lines of therapy was 5 (range: 4 to 13); 83% of patients were refractory to the last line of therapy. Sixty-five percent of patients received prior stem cell transplantation. Seventy-nine percent of patients were triple-class refractory (refractory to a proteasome inhibitor, an immunomodulatory agent, and an anti-CD38 monoclonal antibody). Thirteen percent of patients were previously treated with a BCMA antibody-drug conjugate.

Efficacy was established based on objective response rate (ORR) as determined by blinded independent review committee (IRC), as measured using the International Myeloma Working Group (IMWG) criteria (see Table 10). The median time to first response was 0.95 months (range: 0.5 to 6 months). With a median follow-up of 11.3 months among responders, the estimated duration of response (DOR) rate was 89% (95% CI: 77, 95) at 9 months and 72% (95% CI: 54, 84) at 12 months.

Table 10: Efficacy Results for LINKER-MM1
Efficacy Endpoints | LYNOZYFIC N=80
Objective Response Rate (ORR) % (n) | 70% (56)
(95% CI) | (59,80)
Complete response (CR) or better, % (n) | 45% (36)
(95% CI) | (34,57)
Stringent complete response (sCR), % (n) | 39% (31)
Complete response (CR), % (n) | 6% (5)
Very good partial response (VGPR) % (n) | 19% (15)
Partial response (PR), % (n) | 6% (5)
Duration of Response (DOR) [Based on Kaplan-Meier estimation.]
Median, months (95% CI) | NR (12, NE)
CI=confidence interval; NE=not estimable

16 HOW SUPPLIED/STORAGE AND HANDLING

LYNOZYFIC (linvoseltamab-gcpt) injection is a clear to slightly opalescent, colorless to pale yellow solution in a single-dose vial. It is supplied as provided in Table 11.

Table 11: Packaging Configurations
Carton contents | NDC
One 5 mg/2.5 mL (2 mg/mL) single-dose vial | 61755-054-01
One 200 mg/10 mL (20 mg/mL) single-dose vial | 61755-056-01

STORAGE AND HANDLING

Store unopened vial in a refrigerator at 2°C to 8°C (36°F to 46°F) in the original carton to protect from light. Do not freeze or shake.

17 PATIENT COUNSELING INFORMATION

Advise the patient to read the FDA-approved patient labeling (Medication Guide).

Cytokine Release Syndrome (CRS)

Advise patients that they should be hospitalized for 24 hours after administration of the first and second step-up doses of LYNOZYFIC [see Dosage and Administration (2.2)]. Inform patients of the risk of CRS, and discuss the signs and symptoms associated with CRS, including fever, chills, hypoxia, tachycardia, and hypotension. Counsel patients to seek immediate medical attention should signs or symptoms of CRS occur at any time [see Warnings and Precautions (5.1)].

Neurologic Toxicity, including Immune Effector Cell-Associated Neurotoxicity Syndrome

Discuss the signs and symptoms associated with neurologic toxicity, including ICANS, including confusion, depressed level of consciousness, and lethargy. Advise patients to immediately contact their healthcare provider if they experience any signs or symptoms of neurologic toxicity. Advise patients to refrain from driving, or operating heavy or potentially dangerous machinery, for 48 hours after completion of each of the step-up doses or if they experience new onset of neurologic toxicity symptoms until the symptoms resolve [see Warnings and Precautions (5.2)].

LYNOZYFIC REMS

LYNOZYFIC is available only through a restricted program called the LYNOZYFIC REMS. Inform patients that they will be given a Patient Wallet Card that they should carry with them at all times and show to all of their healthcare providers. This card describes symptoms of CRS and neurologic toxicity, including ICANS which, if experienced, should prompt the patient to seek immediate medical attention [see Warnings and Precautions (5.3)].

Infections

Advise patients of the risk of serious infections. Instruct patients to immediately report infection-related signs or symptoms of infection (e.g., fever, chills, weakness) [see Warnings and Precautions (5.4)].

Neutropenia

Discuss the signs and symptoms associated with neutropenia and febrile neutropenia [see Warnings and Precautions (5.5)].

Hepatotoxicity

Advise patients that liver enzymes elevations may occur and that they should report symptoms that may indicate liver toxicity, including fatigue, anorexia, right upper abdominal discomfort, dark urine, or jaundice [see Warnings and Precautions (5.6)].

Embryo-Fetal Toxicity

Advise pregnant women and females of reproductive potential of the potential risk to a fetus. Advise females of reproductive potential to inform their healthcare provider if they are pregnant or become pregnant. Advise females of reproductive potential to use effective contraception during treatment with LYNOZYFIC and for 3 months after the last dose [see Warnings and Precautions (5.7), Use in Specific Populations (8.1, 8.3)].

Lactation

Advise women not to breastfeed during treatment with LYNOZYFIC and for 3 months after the last dose [see Use in Specific Populations (8.2)].

Manufactured by:
Regeneron Pharmaceuticals, Inc.
777 Old Saw Mill River Road
Tarrytown, NY 10591-6707
U.S. License No. 1760
LYNOZYFIC is a trademark of Regeneron Pharmaceuticals, Inc.

©2025 Regeneron Pharmaceuticals, Inc.
All rights reserved.

MEDICATION GUIDE
LYNOZYFIC™ (lin-oh-ZI-fik)
(linvoseltamab-gcpt)
injection, for intravenous use

What is the most important information I should know about LYNOZYFIC?
LYNOZYFIC may cause serious or life-threatening side effects, including:

- Cytokine Release Syndrome (CRS) and infusion related reactions (IRR). CRS is common during treatment with LYNOZYFIC and can also be serious or life-threatening. Tell your healthcare provider or get medical help right away if you develop any signs or symptoms of CRS or IRR, including:

- fever of 100.4°F (38°C) or higher
- chills or shaking
- trouble breathing

- fast heartbeat
- dizziness or light-headedness

- Neurologic problems. LYNOZYFIC can cause neurologic problems that can be serious or life-threatening. Tell your healthcare provider or get medical help right away if you develop any signs or symptoms of neurologic problems, including:

- headache
- agitation, trouble staying awake, confusion or disorientation, seeing or hearing things that are not real (hallucinations)
- trouble speaking, writing, thinking, remembering things, paying attention, or understanding things

- problems walking, muscle weakness, shaking (tremors), loss of balance, or muscle spasms
- numbness and tingling (feeling like "pins and needles")
- burning, throbbing, or stabbing pain
- changes in your handwriting
- seizures

Due to the risk of CRS and neurologic problems, you will receive LYNOZYFIC on a "step-up dosing schedule" and should be hospitalized for 24 hours after the first and second "step-up" doses.

- During the "step-up dosing schedule":
  - For your first dose, you will receive a smaller "step-up" dose of LYNOZYFIC on Day 1 of your treatment.
  - For your second dose, you will receive a larger "step-up" dose of LYNOZYFIC, which is usually given on Day 8 of your treatment.
  - For your third dose, you will receive the first treatment dose of LYNOZYFIC, which is usually given on Day 15 of your treatment.
- Your healthcare provider may repeat one or both of the "step-up" doses depending on side effects or if your treatment is delayed.
- Before the "step-up" doses and the first two treatment doses of LYNOZYFIC, you will receive medicines to help reduce your risk of CRS and IRR. Your healthcare provider will decide if you need to receive medicine to help reduce your risk of side effects with future doses.
- See "How will I receive LYNOZYFIC?" for more information about how you will receive LYNOZYFIC.

- LYNOZYFIC is available only through the LYNOZYFIC Risk Evaluation and Mitigation Strategy (REMS) due to the risk of side effects of CRS and neurologic problems. You will receive a Patient Wallet Card from your healthcare provider. Carry the LYNOZYFIC Patient Wallet Card with you at all times and show it to all of your healthcare providers. The LYNOZYFIC Patient Wallet Card lists signs and symptoms of CRS and neurologic problems. Get medical help right away if you develop any of the signs and symptoms listed on the LYNOZYFIC Patient Wallet Card. You may need to be treated in a hospital.

Your healthcare provider will monitor you for signs and symptoms of CRS and neurologic problems during treatment with LYNOZYFIC, as well as other side effects, and may treat you in a hospital if needed. Your healthcare provider may temporarily stop or completely stop your treatment with LYNOZYFIC if you develop CRS, neurologic problems, or any other severe side effects.
If you have any questions about LYNOZYFIC, ask your healthcare provider.
See "What are the possible side effects of LYNOZYFIC?" below for more information about side effects.

What is LYNOZYFIC?
LYNOZYFIC is a prescription medicine used to treat adults with multiple myeloma who:

- have already received at least 4 treatment regimens, including a proteasome inhibitor, an immunomodulatory agent and an anti-CD38 monoclonal antibody to treat their multiple myeloma, and
- their cancer has come back or did not respond to prior treatment.

It is not known if LYNOZYFIC is safe and effective in children.

Before receiving LYNOZYFIC, tell your healthcare provider about all of your medical conditions, including if you:

- have an infection.
- are pregnant or plan to become pregnant. LYNOZYFIC may harm your unborn baby. Tell your healthcare provider right away if you become pregnant or think that you may be pregnant during treatment with LYNOZYFIC.
  Females who are able to become pregnant:
  - Your healthcare provider should do a pregnancy test before you start treatment with LYNOZYFIC.
  - You should use an effective form of birth control (contraception) during treatment with LYNOZYFIC and for 3 months after your last dose of LYNOZYFIC.
- are breastfeeding or plan to breastfeed. It is not known whether LYNOZYFIC passes into your breast milk. Do not breastfeed during treatment with LYNOZYFIC and for 3 months after your last dose of LYNOZYFIC.

Tell your healthcare provider about all the medicines you take, including prescription and over-the-counter medicines, vitamins, and herbal supplements.

How will I receive LYNOZYFIC?

- LYNOZYFIC will be given to you by your healthcare provider by infusion through a needle placed in a vein (intravenous infusion).
- See "What is the most important information I should know about LYNOZYFIC?" for more information about how you will receive LYNOZYFIC.
- After the "step-up dosing schedule", the treatment dose of LYNOZYFIC is usually given 1 time each week for 11 doses, and then 1 time every other week for 5 doses. After these doses and based on how your disease responds, your healthcare provider will decide if you are able to receive LYNOZYFIC less often (every 4 weeks) or will continue to have every other week treatment.
- Your healthcare provider will decide how long you will receive treatment with LYNOZYFIC.
- If you miss any appointments, call your healthcare provider as soon as possible to reschedule your appointment. It is important for you to be monitored closely for side effects during treatment with LYNOZYFIC.

What should I avoid while receiving LYNOZYFIC?
Do not drive, or operate heavy or potentially dangerous machinery, or do other dangerous activities for 48 hours after completing each of your "step-up" doses or at any time during treatment with LYNOZYFIC if you develop new neurologic symptoms, until the symptoms go away.
See "What is the most important information I should know about LYNOZYFIC?" for more information about signs and symptoms of neurologic problems.

What are the possible side effects of LYNOZYFIC?
LYNOZYFIC may cause serious side effects, including:

- See "What is the most important information I should know about LYNOZYFIC?"
- Infections. LYNOZYFIC can cause bacterial, viral, or fungal infections that are serious, life-threatening, or that may lead to death. Upper respiratory tract infections and pneumonia are common during treatment with LYNOZYFIC.
  - Your healthcare provider will monitor you for signs and symptoms of infection before and during treatment with LYNOZYFIC.
  - Your healthcare provider may prescribe medicines for you to help prevent infections and treat you as needed if you develop an infection during treatment with LYNOZYFIC.
  - Tell your healthcare provider right away if you develop any signs or symptoms of infection during treatment with LYNOZYFIC, including:

  - fever of 100.4 °F (38 °C) or higher
  - chills
  - cough
  - shortness of breath

  - chest pain
  - sore throat
  - pain during urination
  - feeling weak or generally unwell

- Decreased white blood cell counts. Decreased white blood cell counts are common during treatment with LYNOZYFIC and can also be severe. Fever can happen with low white blood cell counts and may be a sign that you have an infection. Your healthcare provider will check your blood cell counts before you start treatment and during treatment with LYNOZYFIC, and will treat you as needed.
- Liver problems. LYNOZYFIC can cause increased liver enzymes and bilirubin in your blood. These increases can happen with or without you also having CRS. Your healthcare provider will do blood tests to check your liver before starting and during treatment with LYNOZYFIC. Tell your healthcare provider if you develop any of the following signs or symptoms of liver problems:

- tiredness
- loss of appetite
- pain in your right upper stomach-area (abdomen)

- dark urine
- yellowing of your skin or the white part of your eyes

The most common side effects of LYNOZYFIC include:

- muscle and bone pain
- cough
- diarrhea
- tiredness or weakness

- nausea
- headache
- shortness of breath

The most common severe abnormal blood test results with LYNOZYFIC include: low white blood cell counts and low red blood cell counts.
These are not all of the possible side effects of LYNOZYFIC.
Call your doctor for medical advice about side effects. You may report side effects to FDA at 1-800-FDA-1088.

General information about safe and effective use of LYNOZYFIC
Medicines are sometimes prescribed for purposes other than those listed in a Medication Guide. You can ask your pharmacist or healthcare provider for information about LYNOZYFIC that is written for health professionals.

What are the ingredients in LYNOZYFIC?
Active ingredient: linvoseltamab-gcpt
Inactive ingredients: histidine, L-histidine hydrochloride monohydrate, polysorbate 80, sucrose, and Water for Injection.

Manufactured by: Regeneron Pharmaceuticals, Inc., Tarrytown, NY 10591 U.S. License No. 1760
For more information about LYNOZYFIC, go to www.LYNOZYFIC.com or call 1-844-746-4363.
LYNOZYFIC is a trademark of Regeneron Pharmaceuticals, Inc.
© 2025 Regeneron Pharmaceuticals, Inc.
All rights reserved.

This Medication Guide has been approved by the U.S. Food and Drug Administration.

Issued: July 2025

PRINCIPAL DISPLAY PANEL - 5 mg / 2.5 mL Vial Carton

NDC 61755-054-01
Rx only

LYNOZYFIC™
(linvoseltamab-gcpt)
Injection

5 mg / 2.5 mL (2 mg/mL)

For Intravenous Infusion after Dilution

Single-Dose Vial. Discard unused portion.

ATTENTION: Dispense the enclosed Medication Guide
to each patient.

One 2.5 mL Vial
REGENERON

PRINCIPAL DISPLAY PANEL - 200 mg / 10 mL Vial Carton

NDC 61755-056-01
Rx only

LYNOZYFIC™
(linvoseltamab-gcpt)
Injection

200 mg / 10 mL (20 mg/mL)

For Intravenous Infusion after Dilution

Single-Dose Vial. Discard unused portion.

ATTENTION: Dispense the enclosed Medication Guide
to each patient.

One 10 mL Vial
REGENERON